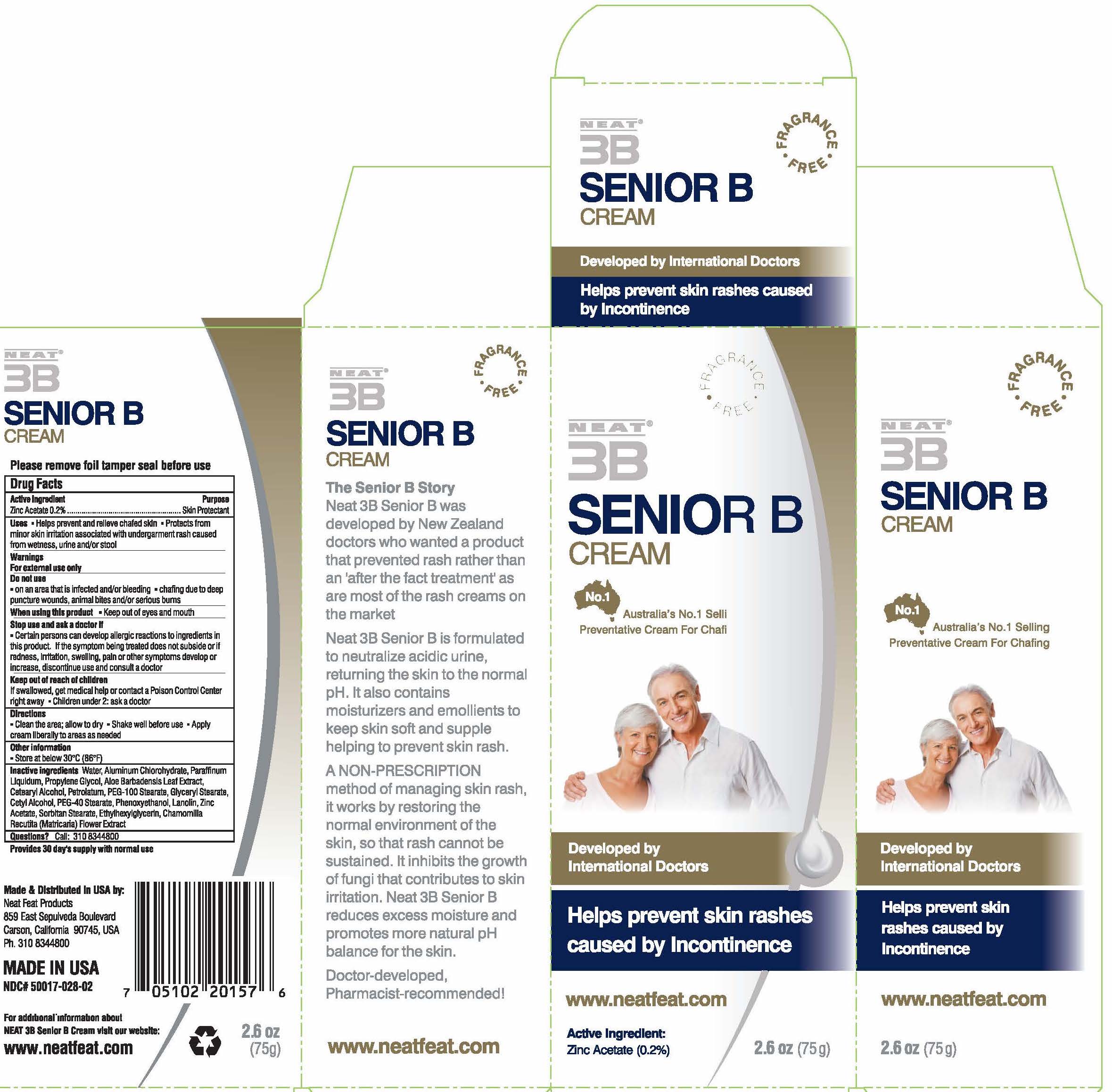 DRUG LABEL: Neat 3B Senior B
NDC: 50017-028 | Form: CREAM
Manufacturer: Neat Feat Products Limited
Category: otc | Type: HUMAN OTC DRUG LABEL
Date: 20231101

ACTIVE INGREDIENTS: ZINC ACETATE 2 mg/1 g
INACTIVE INGREDIENTS: WATER; ALUMINUM CHLOROHYDRATE; MINERAL OIL; POLYETHYLENE GLYCOL, UNSPECIFIED; GLYCERYL MONOSTEARATE; PEG-100 STEARATE; CETOSTEARYL ALCOHOL; PETROLATUM; CETYL ALCOHOL

Neat® 3B Senior B Cream

Drug Facts

Active Ingredient

Zinc Acetate 0.2%

Purpose

Skin Protectant

Uses

- Helps prevent and relieve chafed skin
- Protects from minor skin irritation associated with undergarment rash caused from wetness, urine and/or stool

Warnings

For external use only

Do not use

- on an area that is infected and/or bleeding
- chafing due to deep puncture wounds, animal bites and/or serious burns

When using this product

- Keep out of eyes and mouth

Stop use and ask a doctor if

- Certain persons can develop allergic reactions to ingredients in this product. If the symptom being treated does not subside or if redness, irritation, swelling, pain or other symptoms develop or increase, discontinue use and consult a doctor

Keep out of reach of children

If swallowed, get medical help or contact a Poison Control Center right away

- Children under 2: ask a doctor

Directions

- Clean the area; allow to dry
- Shake well before use
- Apply cream liberally to areas as needed

Other information

- Store at below 30°C (86°F)

Inactive ingredients

Water, Aluminum Chlorohydrate, Mineral Oil, Propylene Glycol, Glyceryl Stearate, PEG-100 Stearate, Cetearyl Alcohol, Petrolatum, Cetyl Alcohol, PEG-40 Stearate, Lanolin, Sorbitan Stearate, Diazolidinyl Urea, Methyl Paraben

Questions?

Call: 310 8344800

Distributed in New Zealand by:
Neat Feat Products Limited
Unit 13, 101-111 Diana Drive
Glenfield, Auckland 1310.

Distributed in USA by:
Neat Feat Products
859 East Sepulveda Boulevard
Carson, California 90745, USA

PRINCIPAL DISPLAY PANEL - 75 g Tube Box

FRAGRANCE
• FREE •

NEAT®
3B

SENIOR B
CREAM

No.1

Australia's No.1 Selling
Preventative Cream For Chafing

Developed by
International Doctors

Helps prevent skin rashes
caused by Incontinence.

www.neatfeat.com

Active Ingredient:
Zinc Acetate (0.2%)

2.6 oz (75g)